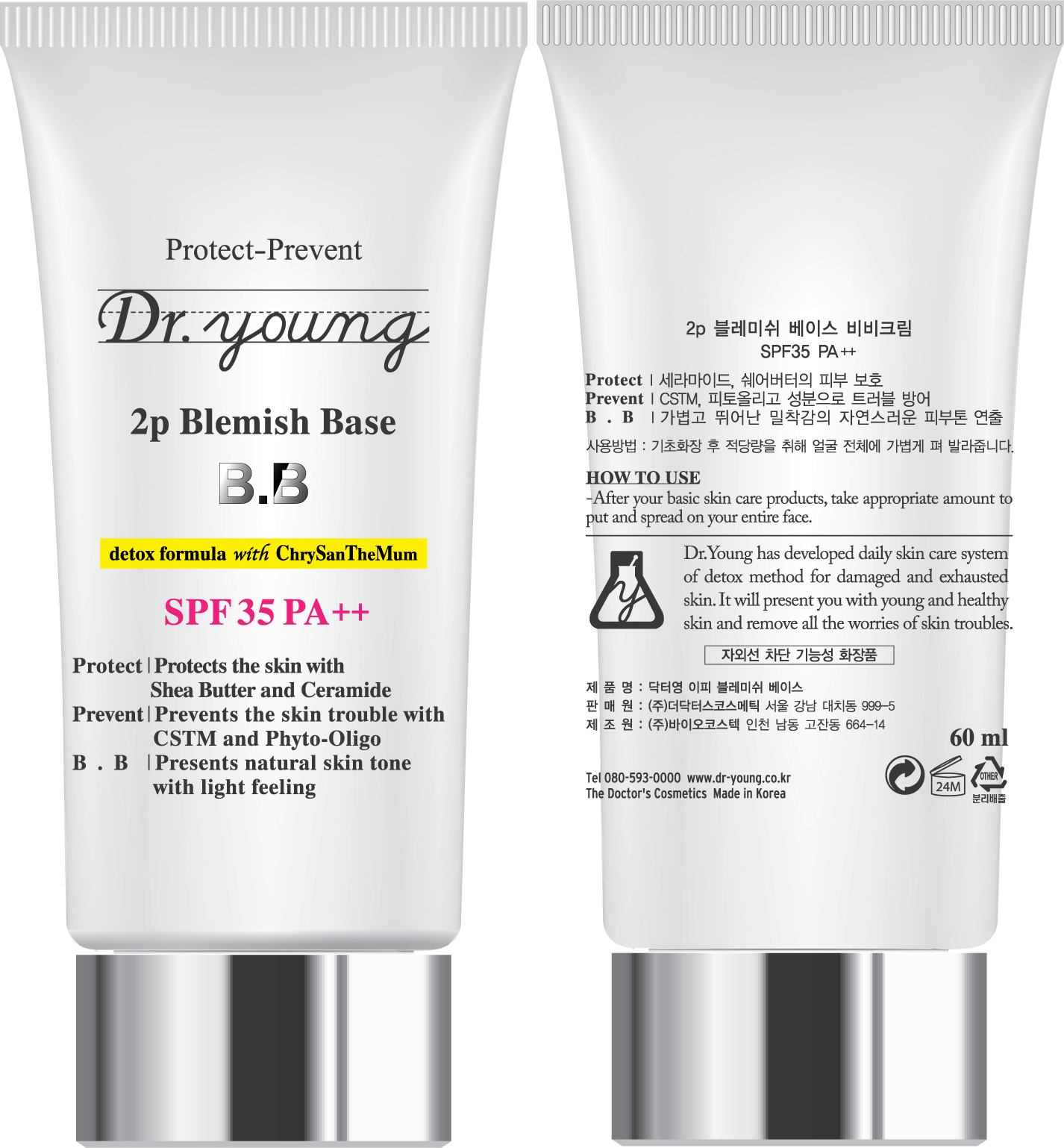 DRUG LABEL: Dr Young 2p Blemish Base SPF35 PA
NDC: 43948-5001 | Form: CREAM
Manufacturer: The Doctor's Cosmetic Inc
Category: otc | Type: HUMAN OTC DRUG LABEL
Date: 20091001

ACTIVE INGREDIENTS: ALLANTOIN 3.6 mL/60 mL

ACTIVE INGREDIENTS:

Chrysanthellum Indicum Extract, Butyrospermum ParkII (Shea Butter), Magnolia Kobus Bark Extract, Camellia Sinensis Leaf Extract, Citrus Grandis (Grapefruit) Fruit Extract, Centella Asiatica Extract, Althaea Rosea Flower Extract, Aloe Barbadensis Leaf Extract, Tocopheryl Acetate, Allantoin, Ceramide 3

CAUTION: Keep away from children

WHEN USING

HOW TO USE:

After your basic skin care products, take appropriate amount to put and spread on your entire face.

PACKAGE LABEL

Label12c